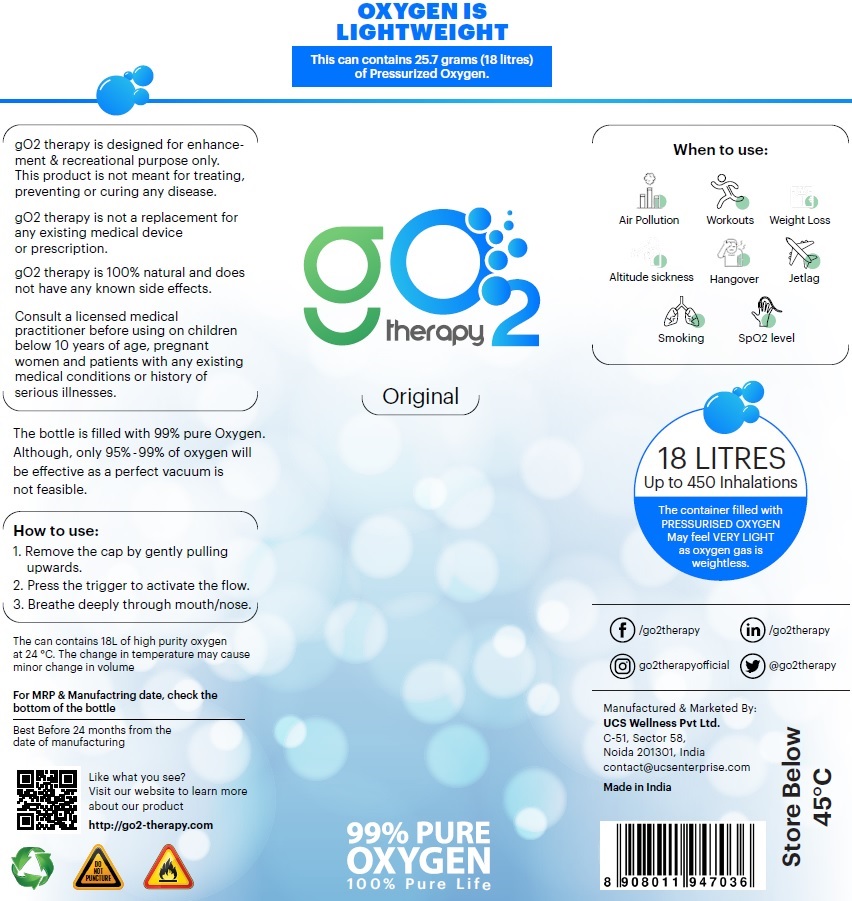 DRUG LABEL: G02 Therapy
NDC: 82007-000 | Form: GAS
Manufacturer: UCS Wellness Private Limited
Category: prescription | Type: HUMAN PRESCRIPTION DRUG LABEL
Date: 20211025

ACTIVE INGREDIENTS: OXYGEN 1 L/1 L

G02 Therapy

pac

gO2 therapy is designed for enhancement & recreational purpose only. This product is not meant for treating, preventing or curing any disease.
gO2 therapy is not a replacement for any existing medical device or prescription.
gO2 therapy is 100% natural and does not have any known side effects.
Consult a licensed medical practitioner before using on children below 10 years of age, pregnant women and patients with any existing medical conditions or history of serious illnesses.

The bottle is filled with 99% pure Oxygen. Although, only 95%-99% of oxygen will be effective as a perfect vacuum is not feasible.

How to use:
1. Remove the cap by gently pulling upwards.
2. Press the trigger to activate the fllow.
3. Breathe deeply through mouth/nose.

The can contains 18L of high purity oxygen at 24 °C. The change in temperature may cause minor change in volume